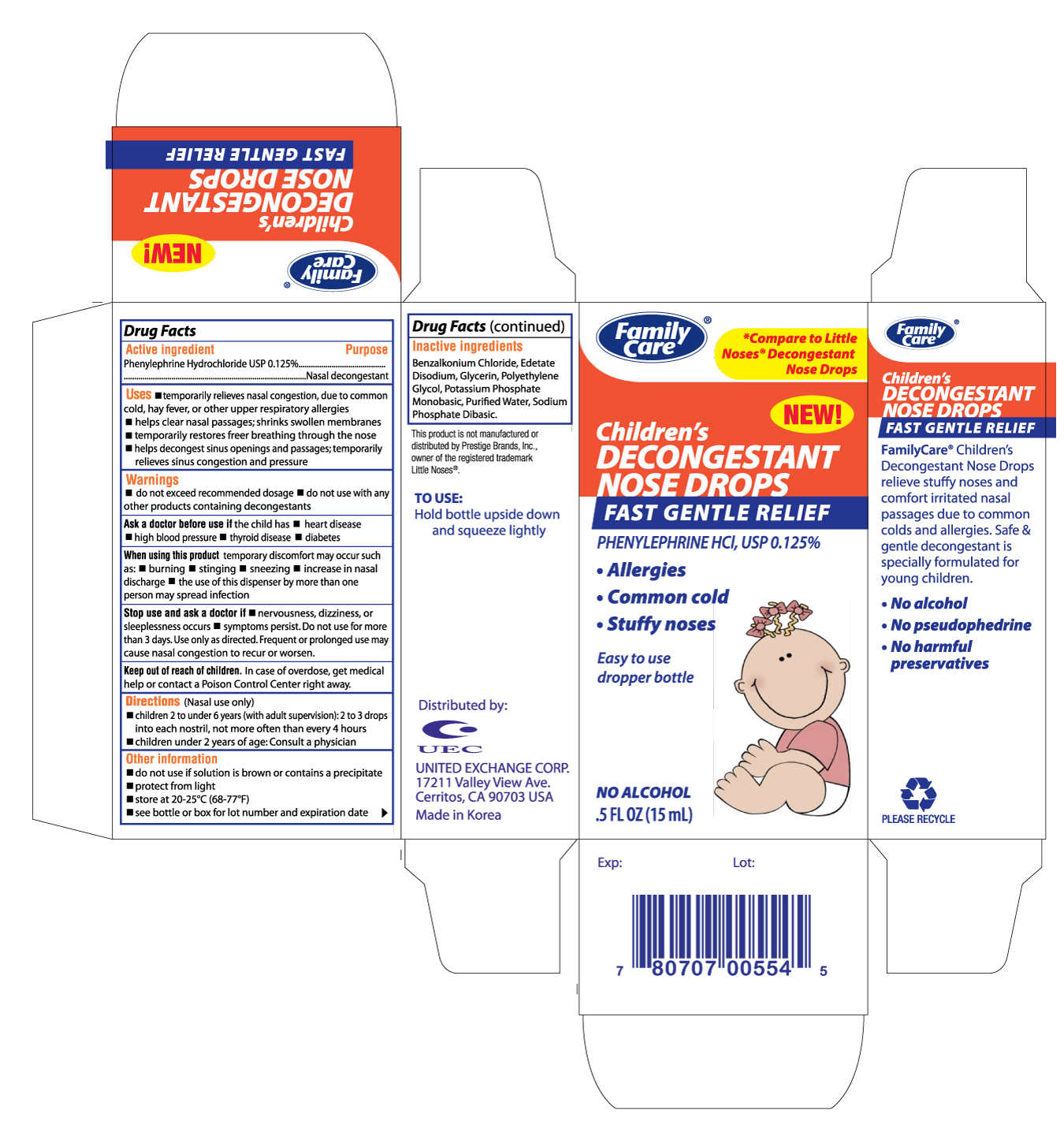 DRUG LABEL: FAMILY CARE CHILDRENS DECONGESTANT NOSE DROPS
NDC: 65923-005 | Form: SOLUTION
Manufacturer: UNITED EXCHANGE CORP
Category: otc | Type: HUMAN OTC DRUG LABEL
Date: 20120110

ACTIVE INGREDIENTS: PHENYLEPHRINE HYDROCHLORIDE 1.25 mg/1 mL
INACTIVE INGREDIENTS: BENZALKONIUM CHLORIDE; EDETATE DISODIUM; GLYCERIN; POLYETHYLENE GLYCOLS; POTASSIUM PHOSPHATE, MONOBASIC; WATER

Drug Facts

Active ingredient Purpose

Phenylephrine Hydrochloride USP 0.125%...................Nasal Decongestant

Uses

- temporarily relieves nasal congestion, due to common cold, hay fever, or other upper respiratory allergies
- helps clear nasal passages; shrinks swollen membranes
- temporarily restores freer breathing through the nose
- helps decongest sinus openings and passages; temporarily relieves sinus congestion and pressure

Warnings

- do not exceed recommended dosage
- do not use with any other products containing decongestants

Ask a doctor before use if the child has

- heart disease
- high blood pressure
- thyroid disease
- diabetes

When using this product temporary discomfort may occur such as:

- burning
- stinging
- sneezing
- increase in nasal discharge
- the use of this dispenser by more than one person may spread infection

Stop use and ask a doctor if

- nervousness, dizziness, or sleeplessness occurs
- symptoms persist. Do not use for more than 3 days. Use only as directed. Frequent or prolonged use may cause nasal congestion to recur or worsen.

Keep out of reach of children. In case of overdose, get medical help or contact a Poison Control Center right away.

INDICATIONS AND USAGE

Directions (Nasal use only)

- children 2 to under 6 years (with adult supervision): 2 to 3 drops into each nostril, not more often than every 4 hours
- children under 2 years of age: Consult a physician

Other information

- do not use if solution is brown or contains a precipitate
- protect from light
- store at 20-25oC (68-77oF)
- see bottle or box for lot number and expiration date

Inactive ingredients

Benzalkonium Chloride, Edetate Disodium, Glycerin, Polyethylene Glycol, Potassium Phosphate Monobasic, Purified Water, Sodium Phosphate Dibasic

DOSAGE AND ADMINISTRATION

Distributed by:

UNITED EXCHANGE CORP.

17211 VALLEY VIEW AVE.

CERRITOS, CA 90703 USA

MADE IN KOREA

PACKAGE LABEL

Enter section text here